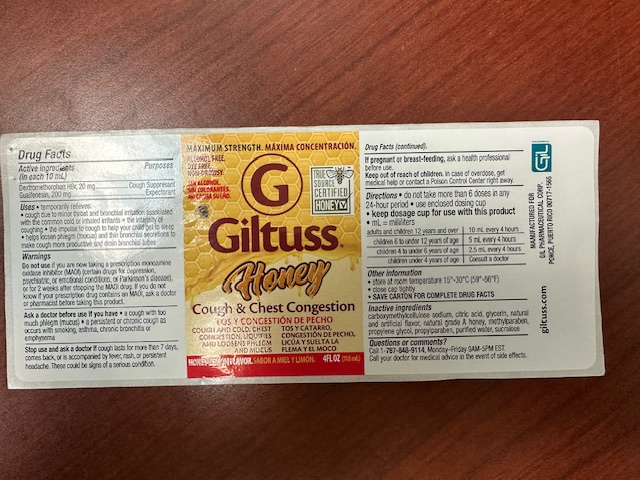 DRUG LABEL: Giltuss Honey Cough and Chest Congestion
NDC: 65852-005 | Form: LIQUID
Manufacturer: Dextrum Laboratories, Inc
Category: otc | Type: HUMAN OTC DRUG LABEL
Date: 20250929

ACTIVE INGREDIENTS: GUAIFENESIN 200 mg/10 mL; DEXTROMETHORPHAN HYDROBROMIDE 20 mg/10 mL
INACTIVE INGREDIENTS: METHYLPARABEN; WATER; PROPYLPARABEN; CARBOXYMETHYLCELLULOSE SODIUM; SUCRALOSE; GLYCERIN; HONEY; CITRIC ACID

Giltuss Honey Cough & Chest Congestiion

Indication and user panel

Indication and user section:

Do not take more than 6 doses in any 24-hours perio. use enclosed dosing cup

- Keep dosage cup for use whit this product
- ml= milliliters

Adults and childrens 12 years and over 10ml every 4 hours

Children 6 to 12 years of age 5 ml every 4 hours

Children 4 to under 6 years of age 2.5ml every 4 hous

Children under 4 yeras of age Consult a doctor

Active ingredient

Acive Ingredient

In each 10 ml

Dextromethorphan HBr 20mg

Guafenesin 200mg

Purposes:

Sough suppresant

Expectorant

Warnings

Do not use if you are now taking a prescription monoamine oxidase inhibidor (MAOI) (Certain drugs for depression, psychiatric or emotional conditions, or Parkinson's desease), or for two weeks after stopping the MAOI drug. If you do not know if you prescription drug constains an MAOI, ask a doctor or pharmacist before taking this product.

Keep out of the reach of the children

In case of overdose, get medical help or contact a poison Control Center right away.

Pregnant or breast feedings

If pregnant or breast-feeding, ask a health professioinal before use.

Dosage and Administration

Dosage

Adults and childrens 12 years and over 10ml every 4 hours

Children 6 to 12 years of age 5 ml every 4 hours

Children 4 to under 6 years of age 2.5ml every 4 hous

Children under 4 yeras of age Consult a doctor

INACTIVE INGREDIENT

Inacyive ingredients

C arboxymethylcellulose sodium, citric acid, glycerin, natural and artificial flavor, , natural grade A honey, methylparaben, propylene glycol,

propylparaben, purified water, sucralose.

Question section

Questions or comments

Call 787-848-9114 Monday-Friday 9AM-5PM EST.

Call your doctor for medical advice in the event of side effects.

Warnings

Do not use if you are now taking a prescription monoamine oxidase inhibidor (MAOI) (Certain drugs for depression, psychiatric or emotional conditions, or Parkinson's desease), or for two weeks after stopping the MAOI drug. If you do not know if you prescription drug constains an MAOI, ask a doctor or pharmacist before taking this product.

principal display panel

Maximum strength. Maxima Concentracion

Alcohol Free

Dye free

Non-Drowsy

True source

Certified Honey

Giltuss Honey Cough % Chest Congestion

Tos y congestion de Pecho

cough and cold, chest Tos y catarro,

Congestion, liquifies Congestion de Pecho,

and loosens phlegm and mucus Licua y suelt LA FLEMA Y EL MOCO

Honey Lemon flavor. Sabor a Miel y limon 4FL OZ (118ml)